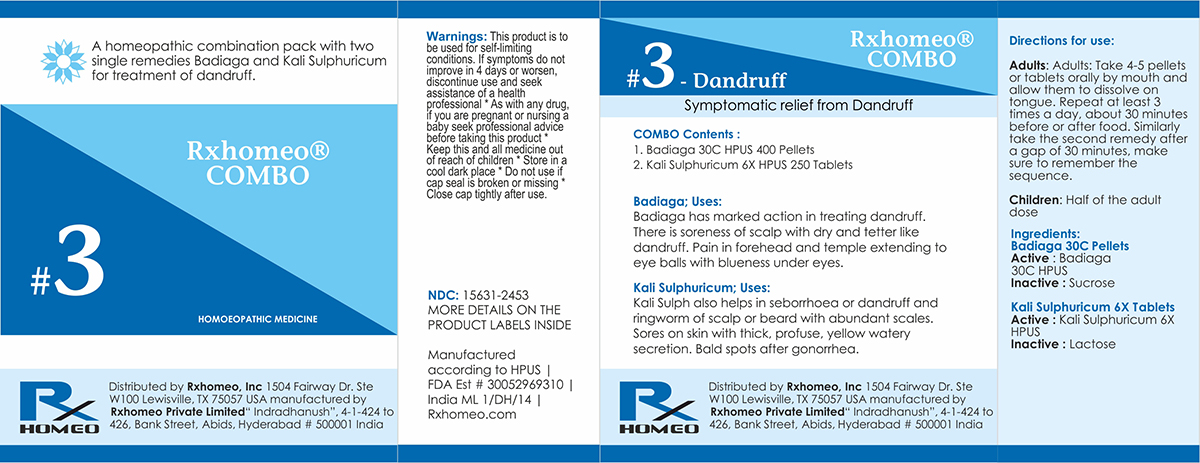 DRUG LABEL: Rxhomeo Homeopathic Combo 3
NDC: 15631-2453 | Form: KIT | Route: ORAL
Manufacturer: Rxhomeo Private Limited d.b.a.
Category: homeopathic | Type: HUMAN OTC DRUG LABEL
Date: 20161021

ACTIVE INGREDIENTS: SPONGILLA LACUSTRIS 2 [hp_X]/1 1; POTASSIUM SULFATE 1 [hp_X]/1 1
INACTIVE INGREDIENTS: SUCROSE; LACTOSE

ACTIVE INGREDIENT

BADIAGA HPUS 2X and higher

KALI SULPHURICUM HPUS 1X and higher

USES

A homeopathic combination pack with two single remedies Badiaga and Kali Sulphuricum for treatment of dandruff.

Badiaga: Badiaga has marked action in treating dandruff. There is soreness of scalp with dry and tetter like dandruff. Pain in forehead and temple extending to eye balls with blueness under eyes.

Kali Sulphuricum: Kali Sulph also helps in seborrhoea or dandruff and ringworm of scalp or beard with abundant scales. Sores on skin with thick, profuse, yellow watery secretion. Bald spots after gonorrhea.

INDICATIONS

Condition listed above or as directed by the physician

DOSAGE

Adults: Take 4-5 pellets or tablets orally by mouth and allow them to dissolve on tongue. Repeat at least 3 times a day, about 30 minutes before or after food. Similarly take the second remedy after a gap of 30 minutes, make sure to remember the sequence.

Children: Half of the adult dose.

WARNINGS

This product is to be used for self-limiting conditions

STOP USE

If symptoms do not improve in 4 days, or worsen, discontinue use and seek assistance of health professional

KEEP OUT OF REACH OF CHILDREN

Keep this and all medication out of reach of children

Do not use if capseal is broken or missing.

Close the cap tightly after use.

INACTIVE INGREDIENTS

Sucrose for Pellets.

Lactose for Tablets.

STORAGE

Store in a cool dark place

QUESTIONS OR COMMENTS

www.Rxhomeo.com | 1.888.2796642 | info@rxhomeo.com
Rxhomeo, Inc 1504 Fairway Dr. Ste W 100 Lewisville, TX 75057 USA